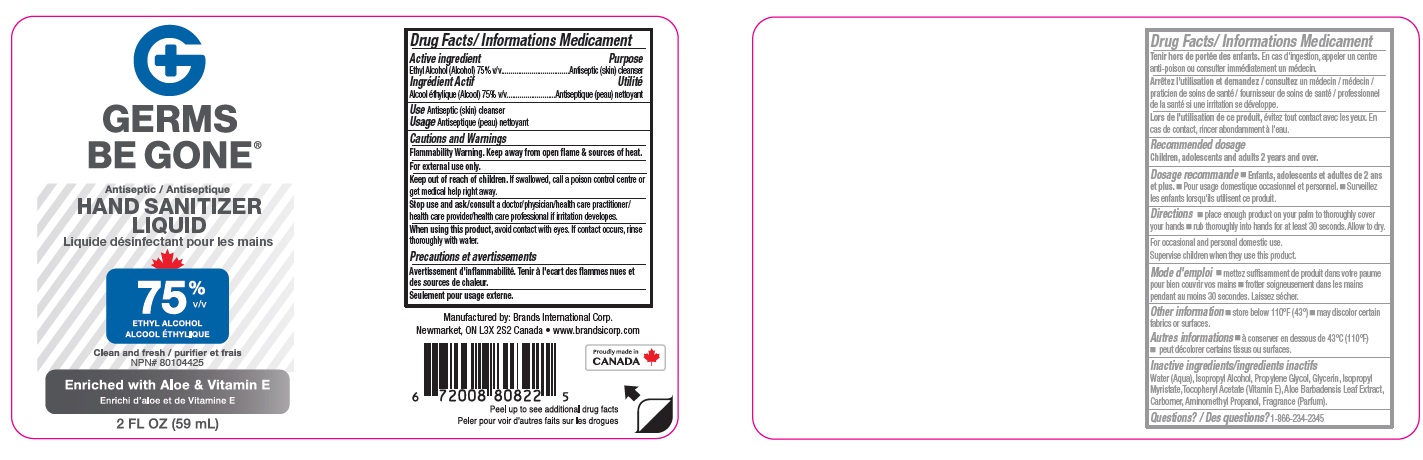 DRUG LABEL: Germs be gone hand Sanitizer
NDC: 50157-520 | Form: LIQUID
Manufacturer: Brands International
Category: otc | Type: HUMAN OTC DRUG LABEL
Date: 20210407

ACTIVE INGREDIENTS: ALCOHOL 75 mL/100 mL
INACTIVE INGREDIENTS: ISOPROPYL MYRISTATE; WATER; ISOPROPYL ALCOHOL; PROPYLENE GLYCOL; CARBOMER INTERPOLYMER TYPE A (ALLYL SUCROSE CROSSLINKED); GLYCERIN; ALOE VERA LEAF; AMINOMETHYLPROPANOL; .ALPHA.-TOCOPHEROL ACETATE

Germs Be Gone Hand sanitizer

Drug Facts

Active Ingredient

Ethyl Alcohol, 75% v/v

Purpose

Antiseptic (skin) clenser

Uses

- Antiseptic (skin) clenser

Warnings

For external use only. Flammable, keep away from fire or flame.

When using this product keep out of eyes. Avoid contact with eyes. If contact with eyes occurs, rinse thoroughly with water.

Stop use and ask a doctor if irritation develops.

Keep out of reach of children. If swallowed, get medical help or contact a Poison Control Center right away.

Directions

- For occasional and personal domestic use.
- Rub thoroughly into hands for at least 30 secoand Allow to dry.
- Supervise children in the use of this product.

Other Information

- Store below 43°C (110°F)
- may discolor certain fabrics or surfaces

Inactive Ingredients

carbomer, aloe barbadensis leaf juice, aminomethyl propanol, glycerin, propylene glycol, water, isopropyl myristate, tocopheryl acetate (Vit E).

Please see label on the container.